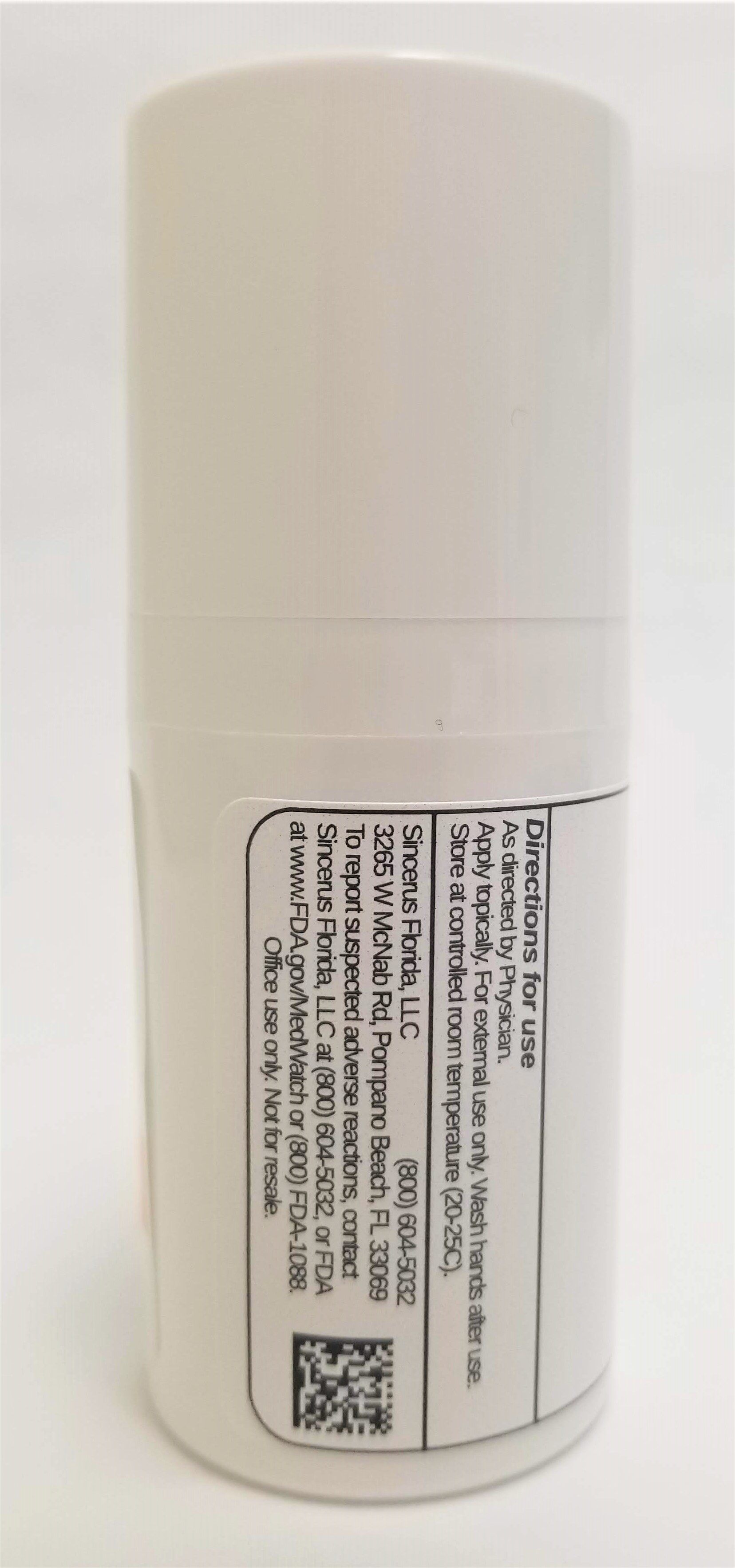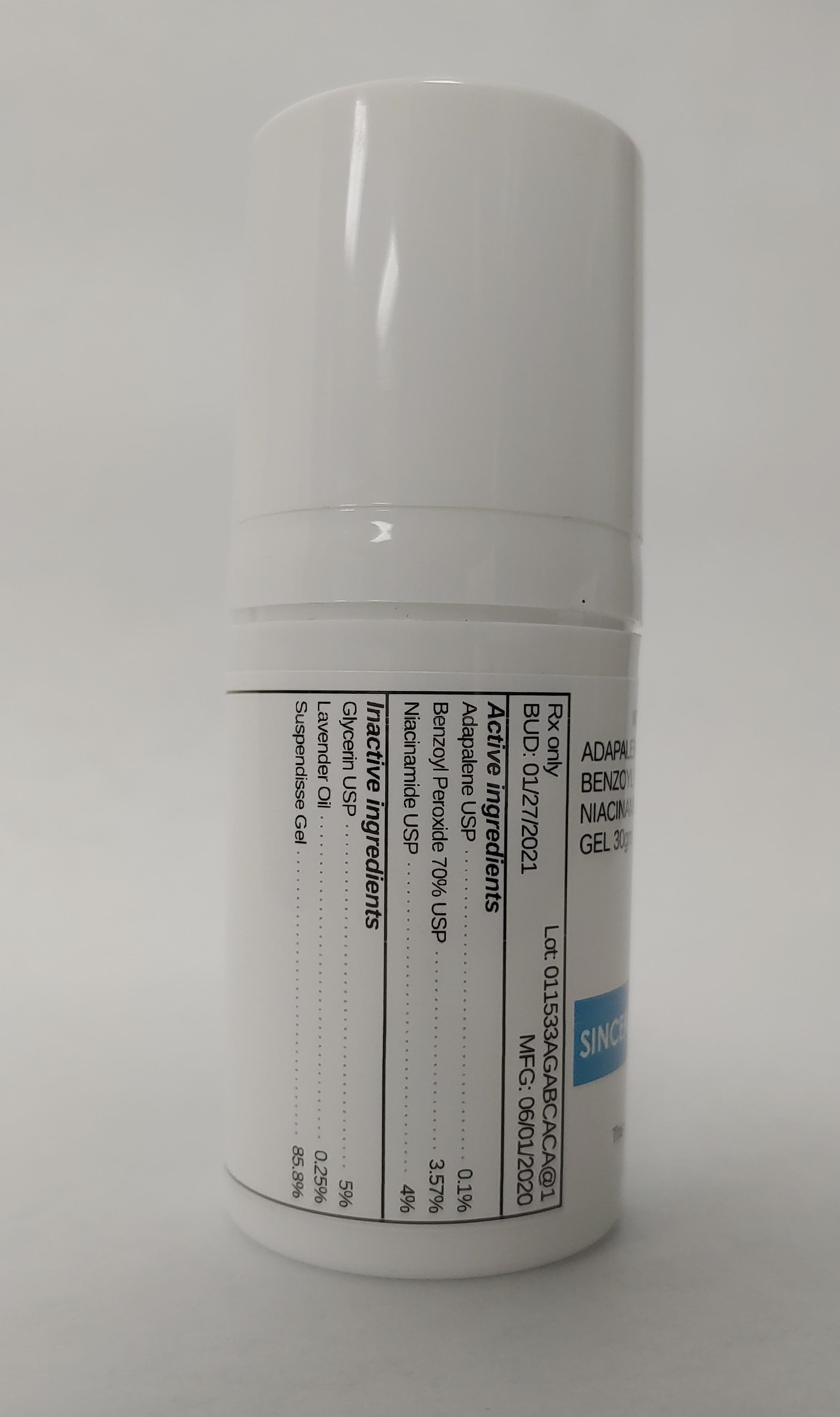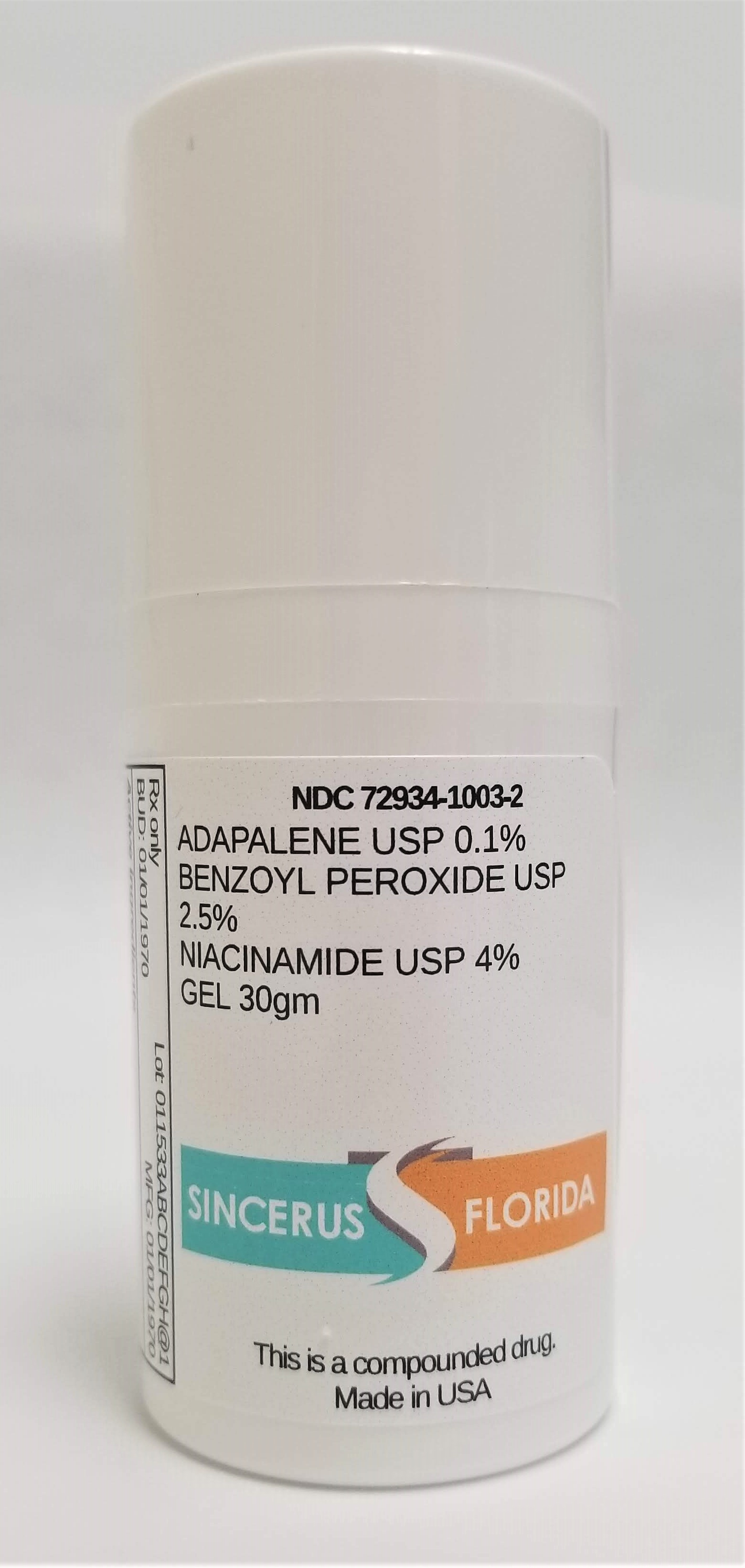 DRUG LABEL: ADAPALENE 0.1% / BENZOYL PEROXIDE 2.5% / NIACINAMIDE 4%
NDC: 72934-1003 | Form: GEL
Manufacturer: Sincerus Florida, LLC
Category: prescription | Type: HUMAN PRESCRIPTION DRUG LABEL
Date: 20200603

ACTIVE INGREDIENTS: ADAPALENE 0.1 g/100 g; BENZOYL PEROXIDE 2.5 g/100 g; NIACINAMIDE 4 g/100 g

ADAPALENE 0.1% / BENZOYL PEROXIDE 2.5% / NIACINAMIDE 4%